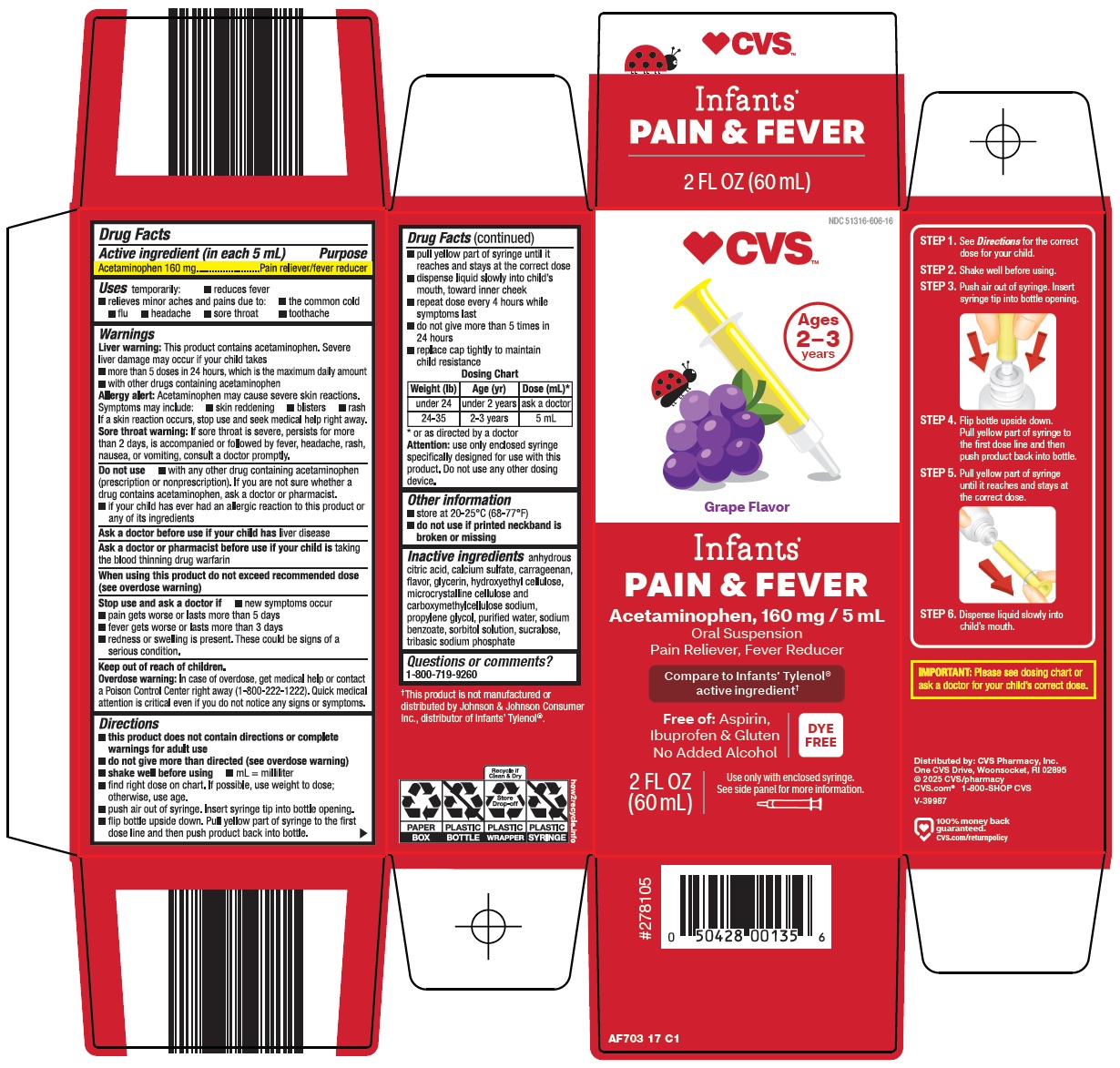 DRUG LABEL: infants pain and fever
NDC: 51316-606 | Form: SUSPENSION
Manufacturer: CVS WOONSOCKET PRESCRIPTION CENTER, INCORPORATED
Category: otc | Type: HUMAN OTC DRUG LABEL
Date: 20251028

ACTIVE INGREDIENTS: ACETAMINOPHEN 160 mg/5 mL
INACTIVE INGREDIENTS: ANHYDROUS CITRIC ACID; CALCIUM SULFATE, UNSPECIFIED FORM; CARRAGEENAN; GLYCERIN; HYDROXYETHYL CELLULOSE, UNSPECIFIED; MICROCRYSTALLINE CELLULOSE; CARBOXYMETHYLCELLULOSE SODIUM, UNSPECIFIED; PROPYLENE GLYCOL; WATER; SODIUM BENZOATE; SORBITOL; SUCRALOSE; SODIUM PHOSPHATE, TRIBASIC

CVS Pharmacy, Inc. Infants’ Pain & Fever Drug Facts

Active ingredient (in each 5 mL)

Acetaminophen 160 mg

Purpose

Pain reliever/fever reducer

Uses

temporarily:

- reduces fever
- relieves minor aches and pains due to:
- the common cold
- flu
- headache
- sore throat
- toothache

Warnings

Liver warning: This product contains acetaminophen. Severe liver damage may occur if your child takes

- more than 5 doses in 24 hours, which is the maximum daily amount
- with other drugs containing acetaminophen

Allergy alert: Acetaminophen may cause severe skin reactions. Symptoms may include:

- skin reddening
- blisters
- rash

If a skin reaction occurs, stop use and seek medical help right away.

Sore throat warning: If sore throat is severe, persists for more than 2 days, is accompanied or followed by fever, headache, rash, nausea, or vomiting, consult a doctor promptly.

Do not use

- with any other drug containing acetaminophen (prescription or nonprescription). If you are not sure whether a drug contains acetaminophen, ask a doctor or pharmacist.
- if your child has ever had an allergic reaction to this product or any of its ingredients

Ask a doctor before use if your child has

liver disease

Ask a doctor or pharmacist before use if your child is

taking the blood thinning drug warfarin

When using this product

do not exceed recommended dose (see overdose warning)

Stop use and ask a doctor if

- pain gets worse or lasts more than 5 days
- fever gets worse or lasts more than 3 days
- new symptoms occur
- redness or swelling is present. These could be signs of a serious condition.

Keep out of reach of children.

Overdose warning: In case of overdose, get medical help or contact a Poison Control Center right away (1-800-222-1222). Quick medical attention is critical even if you do not notice any signs or symptoms.

Directions

- this product does not contain directions or complete warnings for adult use
- do not give more than directed (see overdose warning)
- shake well before using
- mL = milliliter
- find right dose on chart. If possible, use weight to dose; otherwise, use age.
- push air out of syringe. Insert syringe tip into bottle opening.
- flip bottle upside down. Pull yellow part of syringe to the first dose line and then push product back into bottle.
- pull yellow part of syringe until it reaches and stays at the correct dose
- dispense liquid slowly into child’s mouth, toward inner cheek
- repeat dose every 4 hours while symptoms last
- do not give more than 5 times in 24 hours
- replace cap tightly to maintain child resistance

Dosing Chart
Weight (lb) | Age (yr) | Dose (mL)*
under 24 | under 2 years | ask a doctor
24-35 | 2-3 years | 5 mL

* or as directed by a doctor

Attention: use only enclosed syringe specifically designed for use with this product. Do not use any other dosing device.

Other information

- store at 20-25°C (68-77°F)
- do not use if printed neckband is broken or missing

Inactive ingredients

anhydrous citric acid, calcium sulfate, carrageenan, flavor, glycerin, hydroxyethyl cellulose, microcrystalline cellulose and carboxymethylcellulose sodium, propylene glycol, purified water, sodium benzoate, sorbitol solution, sucralose, tribasic sodium phosphate

Questions or comments?

1-800-719-9260

Package/Label Principal Display Panel

CVS™

Ages 2-3 years

Grape Flavor

Infants’

PAIN & FEVER

Acetaminophen, 160 mg / 5 mL

Oral Suspension

Pain Reliever, Fever Reducer

Compare to Infants’ Tylenol® active ingredient

Free of: Aspirin, Ibuprofen & Gluten

No Added Alcohol

DYE FREE

2 FL OZ (60 mL)

Use only with enclosed syringe. See side panel for more information.